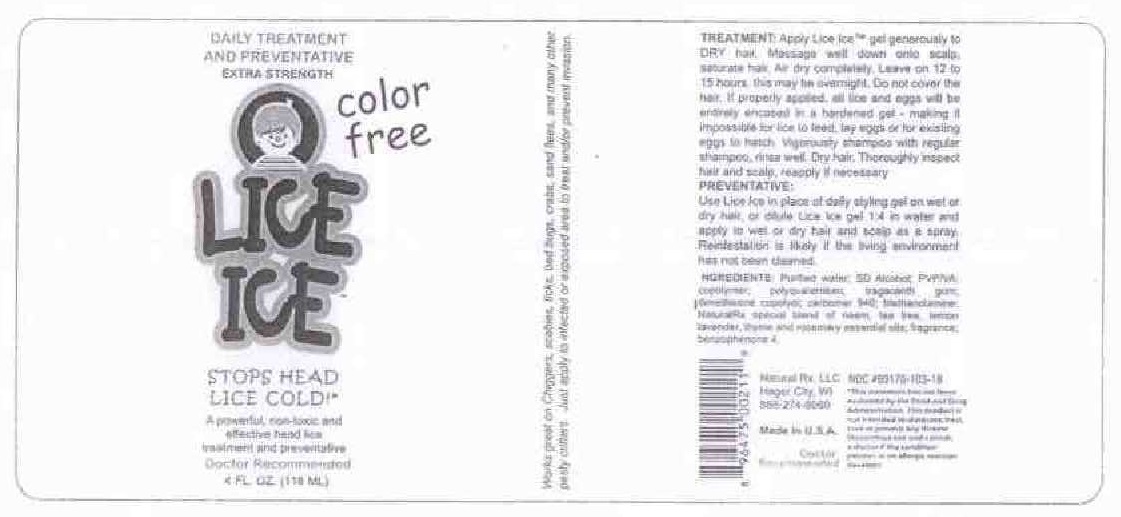 DRUG LABEL: LICE ICE
NDC: 69170-103 | Form: GEL
Manufacturer: NATURALRX LLC
Category: homeopathic | Type: HUMAN OTC DRUG LABEL
Date: 20200323

ACTIVE INGREDIENTS: AZADIRACHTA INDICA SEED OIL 0.937 [hp_X]/100 mL; TEA TREE OIL 0.937 [hp_X]/100 mL
INACTIVE INGREDIENTS: LEMON OIL; LAVENDER OIL; THYME OIL; ROSEMARY OIL; WATER; ALCOHOL; COPOVIDONE K25-31; POLYQUATERNIUM-11 (1000000 MW); TRAGACANTH; DIMETHICONE; CARBOMER 940; TROLAMINE; SULISOBENZONE

NATURALRX - ICE 'EM ALL - COLOR-FREE

ACTIVE INGREDIENTS

NEEM OIL.....0.937 X

TEA TREE OIL.....0.937 X

PURPOSE

LICE TREATMENT

WARNINGS

FOR EXTERNAL USE ONLY

KEEP OUT OF REACH OF CHILDREN.

USES

TREATS HEAD LICE

DIRECTIONS

TREATMENT: APPLY LICE ICE GEL GENEROUSLY TO DRY HAIR. MASSAGE WELL DOWN INTO SCALP AND ROOTS, MAKING SURE TO GET ALL THE HAIR ENCASSED IN THE GEL. ALLOW LICE ICE TO AIR DRY COMPLETELY. LEAVE ON 12 TO 15 HOURS. DO NOT COVER THE HAIR. IF PROPERLY APPLIED, ALL LICE AND EGGS WILL BE ENTIRELY ENCASED IN A HARDENED GEL, MAKING IT IMPOSSIBLE FOR LICE TO FEED, LAY EGGS, OR FOR EGGS TO HATCH. VIGOROUSLY SHAMPOO WITH REGULAR SHAMPOO, RINSE WELL. DRY HAIR. THOROUGHLY INSPECT HAIR AND SCALP, REAPPLY IF NECESSARY.

PREVENTATIVE:

USE LICE INE IN PLACE OF DAILY STYLING GEL ON WET OR DRY HAR OR DILUTE LICE ICE GEL 1:4 IN WATER AND APPLY TO WET OR DRY HAIR AND SCALP AS A SPRAY. REINFESTATION IS LIKELY IF THE LIVING ENVIRONMENT HAS NOT BEEN CLEANED. PLEASE VISIT WWW.LICEICE.COM FOR MORE INFO.

INGREDIENTS:

PURIFIED WATER, SD ALCOHOL, PVP/VA COPOLYMER, POLYQUATERNIUM 11, TRAGACANTH GUM, DIMETHICONE COPOLYOL, CARBOMER 940, TRIETHANOLAMINE, EMPIRE ORGANICS SPECIAL BLEND OF NEEM, TEA TREE, LEMON, LAVENDER, THYME AND ROSEMARY ESSENTIAL OILS, FD&C BLUE NO. 1, FRAGRANCE, BENZOPHENONE 4.